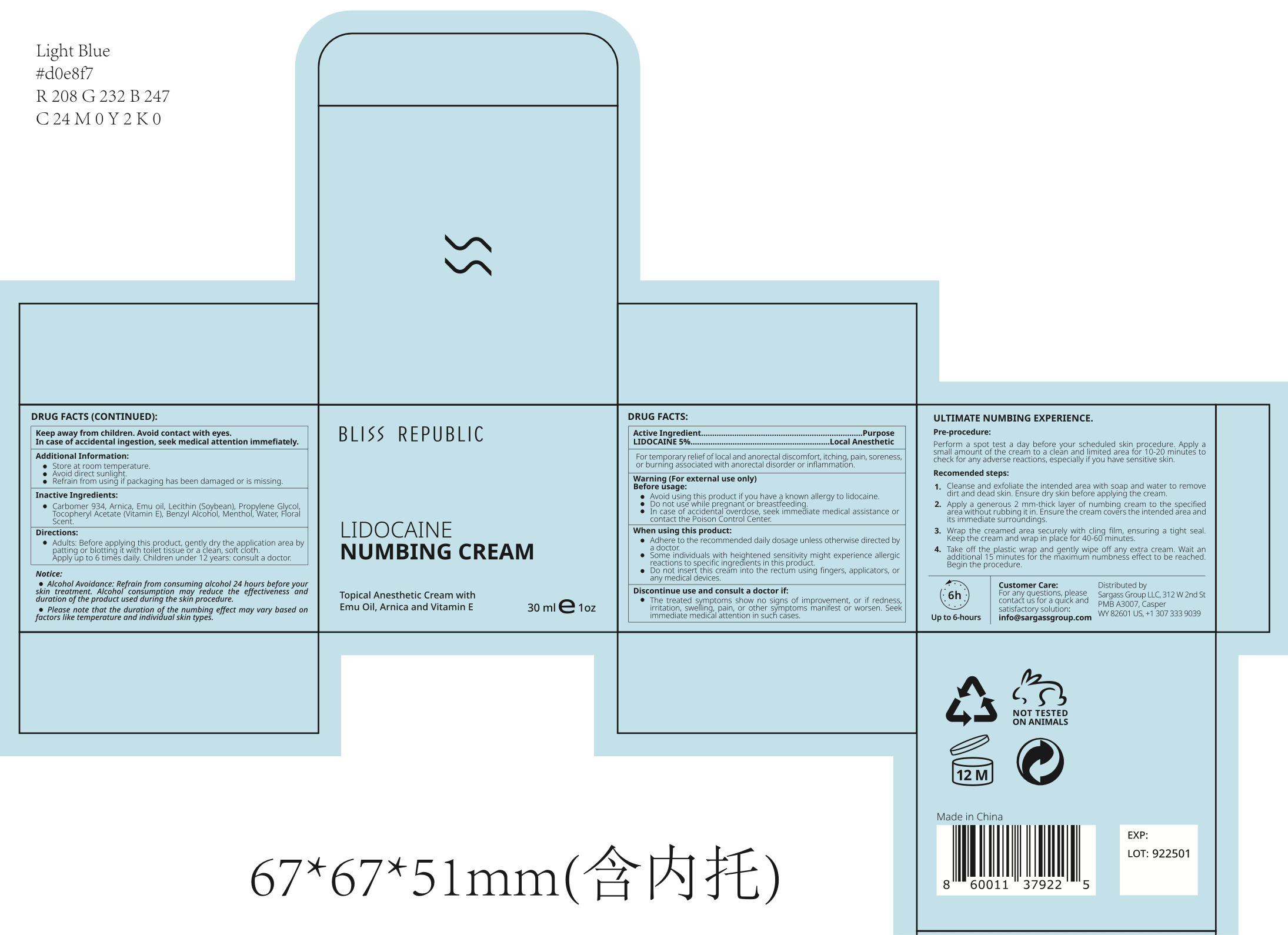 DRUG LABEL: Bliss Republic Lidocaine Numbing Cream
NDC: 84028-111 | Form: CREAM
Manufacturer: Sargass Group Limited Liability Company
Category: otc | Type: HUMAN OTC DRUG LABEL
Date: 20240216

ACTIVE INGREDIENTS: LIDOCAINE HYDROCHLORIDE 5 mg/100 mL
INACTIVE INGREDIENTS: WATER; LECITHIN, SOYBEAN; MENTHOL; CARBOMER 934; ALPHA-TOCOPHEROL ACETATE; ARNICA MONTANA FLOWER; PROPYLENE GLYCOL; BENZYL ALCOHOL

BLISS REPUBLIC LIDOCAINE NUMBING CREAM

Active Ingredient(s)

LIDOCAINE 5%_ _ _ _ _ _ _ _ _ _ _ _ _ _ _ _ _ _ _ _ _ _ Local Anesthetic

Purpose

Topical Anesthetic

Use

For temporary relief of local and anorectal discomfort, itching, pain, soreness, or burning associated with anorectal disorder or inflammation.

Warnings

(For external use only)

Before usage:

Avoid using this product if you have a known allergy to lidocaine.
Do not use while pregnant or breastfeeding.

In case of accidental overdose, seek immediate medical assistance or contact the Poison Control Center.

When using this product:

Adhere to the recommended daily dosage unless otherwise directed by a doctor.
Some individuals with heightened sensitivity might experience allergic reactions to specific ingredients in this product.

Do not insert this cream into the rectum using fingers, applicators, or any medical devices.

KEEP OUT OF REACH OF CHILDREN

Keep away from children. Avoid contact with eyes. In case of accidental ingestion, seek medical attention immefiately.

Discontinue use and consult a doctor if:

The treated symptoms show no signs of improvement, or if redness, irritation, swelling, pain, or other symptoms manifest or worsen. Seek immediate medical attention in such cases.

Directions

Adults: Before applying this product, gently dry the application area by patting or blotting it with toilet tissue or a clean, soft cloth.

Apply up to 6 times daily. Children under 12 years: consult a doctor.

Other information

Additional Information:

Store at room temperature. Avoid direct sunlight. Refrain from using if packaging has been damaged or is missing.

Inactive ingredients

Carbomer 934, Arnica, Emu oil, Lecithin (Soybean), Propylene Glycol, Tocopheryl Acetate (Vitamin E), Benzyl Alcohol, Menthol, Water Floral scent

RECENT MAJOR CHANGES

Notice:

· Alcohol Avoidance: Refrain from consuming alcohol 24 hours before your skin treatment. Alcohol consumption may reduce the effectiveness and duration of the product used during the skin procedure.

· Please note that the duration of the numbing effect may vary based on factors like temperature and individual skin types.

Ultimate Numbing Experience

Recommended steps:

Perform a spot test a day before your scheduled skin procedure. Apply a small amount of the cream to a clean and limited area for 10-20 minutes to check for any adverse reactions, especially if you have sensitive skin.
Cleanse and exfoliate the intended area with soap and water to remove dirt and dead skin. Ensure dry skin before applying the cream.
Apply a generous 2 mm-thick layer of numbing cream to the specified area without rubbing it in. Ensure the cream covers the intended area and its immediate surroundings.
Wrap the creamed area securely with cling film, ensuring a tight seal. Keep the cream and wrap in place for 40-60 minutes.
Take off the plastic wrap and gently wipe off any extra cream. Wait an additional 15 minutes for the maximum numbness effect to be reached. Begin the procedure.

Customer Care:

For any questions, please contact us for a quick and satisfactory solution:

info@sargassgroup.com

Distributed by Sargass Group LLC, Casper, WY 82601

312 W 2nd St, A3007

+1 307 333 9039

Package Label - Principal Display Panel

30mL NDC: 84028-111-11